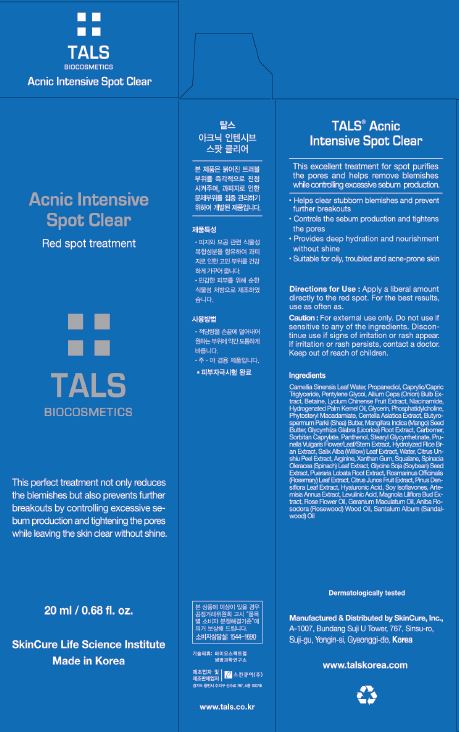 DRUG LABEL: TALS Acnic Intensive Spot Clear
NDC: 72289-0008 | Form: LIQUID
Manufacturer: SKINCURE INC
Category: otc | Type: HUMAN OTC DRUG LABEL
Date: 20190224

ACTIVE INGREDIENTS: GLYCERIN 1.6 g/100 mL
INACTIVE INGREDIENTS: PANTHENOL; NIACINAMIDE; WATER

Drug Facts

ACTIVE INGREDIENT

glycerin

INACTIVE INGREDIENT

Camellia Sinensis Leaf Water
Propanediol
Caprylic/Capric Triglyceride
Pentylene Glycol
Allium Cepa (Onion) Bulb Extract
Betaine
Lycium Chinense Fruit Extract
Niacinamide
Hydrogenated Palm Kernel Oil
Glycerin
Phosphatidylcholine
Phytosteryl Macadamiate
Centella Asiatica Extract
Butyrospermum Parkii (Shea) Butter
Mangifera Indica (Mango) Seed Butter
Glycyrrhiza Glabra (Licorice) Root Extract
Carbomer
Sorbitan Caprylate
Panthenol
Stearyl Glycyrrhetinate
Prunella Vulgaris Flower/Leaf/Stem Extract
Hydrolyzed rice bran extract
Salix Alba (Willow) Leaf Extract
Water(Aqua)
Citrus Unshiu Peel Extract
Arginine
Xanthan Gum
Squalane
Spinacia Oleracea (Spinach) Leaf Extract
Glycine Soja (Soybean) Seed Extract
Pueraria Lobata Root Extract
Rosmarinus Officinalis (Rosemary) Leaf Extract
Citrus Junos Fruit Extract
Pinus Densiflora Leaf Extract
Hyaluronic Acid
Soy Isoflavones
Artemisia Annua Extract
Levulinic Acid
Magnolia Liliflora Bud Extract
Aniba Rosodora (Rosewood) Wood Oil
Geranium Maculatum Oil
Santalum Album (Sandalwood) Oil
Rose Flower Oil

PURPOSE

helps clear stubborn blemishes and prevent further breakouts

controls sebum production and tightens the pores

provides deep hydration and nourishment without shine

suitable for oily, troubled and acne-prone skin

keep out of reach of the children

INDICATIONS AND USAGE

Apply a liberal amount directly to the red spot. For the best results, use as often as.

WARNINGS

for external use only

do not use if sensitive to any of the ingredients

discontinue use if signs of irritation or rash appear

if irritation or rash persists, contact a doctor

DOSAGE AND ADMINISTRATION

for external use only